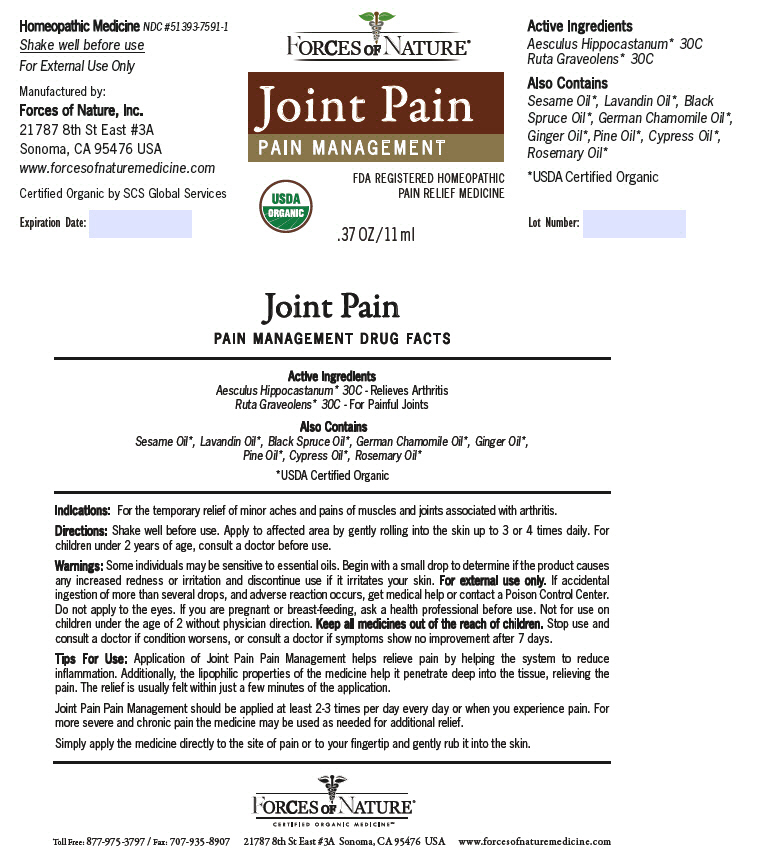 DRUG LABEL: Joint Pain 
NDC: 51393-7591 | Form: SOLUTION/ DROPS
Manufacturer: Forces of Nature
Category: homeopathic | Type: HUMAN OTC DRUG LABEL
Date: 20221025

ACTIVE INGREDIENTS: Aesculus Hippocastanum Whole 30 [hp_C]/1000 mL; Ruta Graveolens Whole 30 [hp_C]/1000 mL
INACTIVE INGREDIENTS: Sesame Oil; Lavandin Oil; Picea Mariana Leaf Oil; Chamomile Flower Oil; Ginger Oil; Pine Needle Oil (Pinus Sylvestris); Cupressus Sempervirens Leaf Oil; Rosemary Oil

Joint Pain
Pain Management

PAIN MANAGEMENT DRUG FACTS

ACTIVE INGREDIENT

PURPOSE

Active Ingredients

Aesculus Hippocastanum [USDA Certified Organic] 30C - Relieves Arthritis

Ruta Graveolens 30C - For Painful Joints

Also Contains

Sesame Oil, Lavandin Oil, Black Spruce Oil, German Chamomile Oil, Ginger Oil, Pine Oil, Cypress Oil, Rosemary Oil

Indications

For the temporary relief of minor aches and pains of muscles and joints associated with arthritis.

Directions

Shake well before use. Apply to affected area by gently rolling into the skin up to 3 or 4 times daily. For children under 2 years of age, consult a doctor before use.

Warnings

Some individuals may be sensitive to essential oils. Begin with a small drop to determine if the product causes any increased redness or irritation and discontinue use if it irritates your skin. For external use only. If accidental ingestion of more than several drops, and adverse reaction occurs, get medical help or contact a Poison Control Center. Do not apply to the eyes. If you are pregnant or breast-feeding, ask a health professional before use. Not for use on children under the age of 2 without physician direction.

KEEP OUT OF REACH OF CHILDREN

Keep all medicines out of the reach of children. Stop use and consult a doctor if condition worsens, or consult a doctor if symptoms show no improvement after 7 days.

Tips For Use

Application of Joint Pain Pain Management helps relieve pain by helping the system to reduce inflammation. Additionally, the lipophilic properties of the medicine help it penetrate deep into the tissue, relieving the pain. The relief is usually felt within just a few minutes of the application.

Joint Pain Pain Management should be applied at least 2-3 times per day every day or when you experience pain. For more severe and chronic pain the medicine may be used as needed for additional relief.

Simply apply the medicine directly to the site of pain or to your fingertip and gently rub it into the skin.

Manufactured by:
Forces of Nature, Inc.
21787 8th St East #3A
Sonoma, CA 95476 USA

PRINCIPAL DISPLAY PANEL - 11 ml Bottle Label

FORCES OF NATURE®

Joint Pain
PAIN MANAGEMENT

FDA REGISTERED HOMEOPATHIC
PAIN RELIEF MEDICINE

USDA
ORGANIC

.37 OZ/11 ml